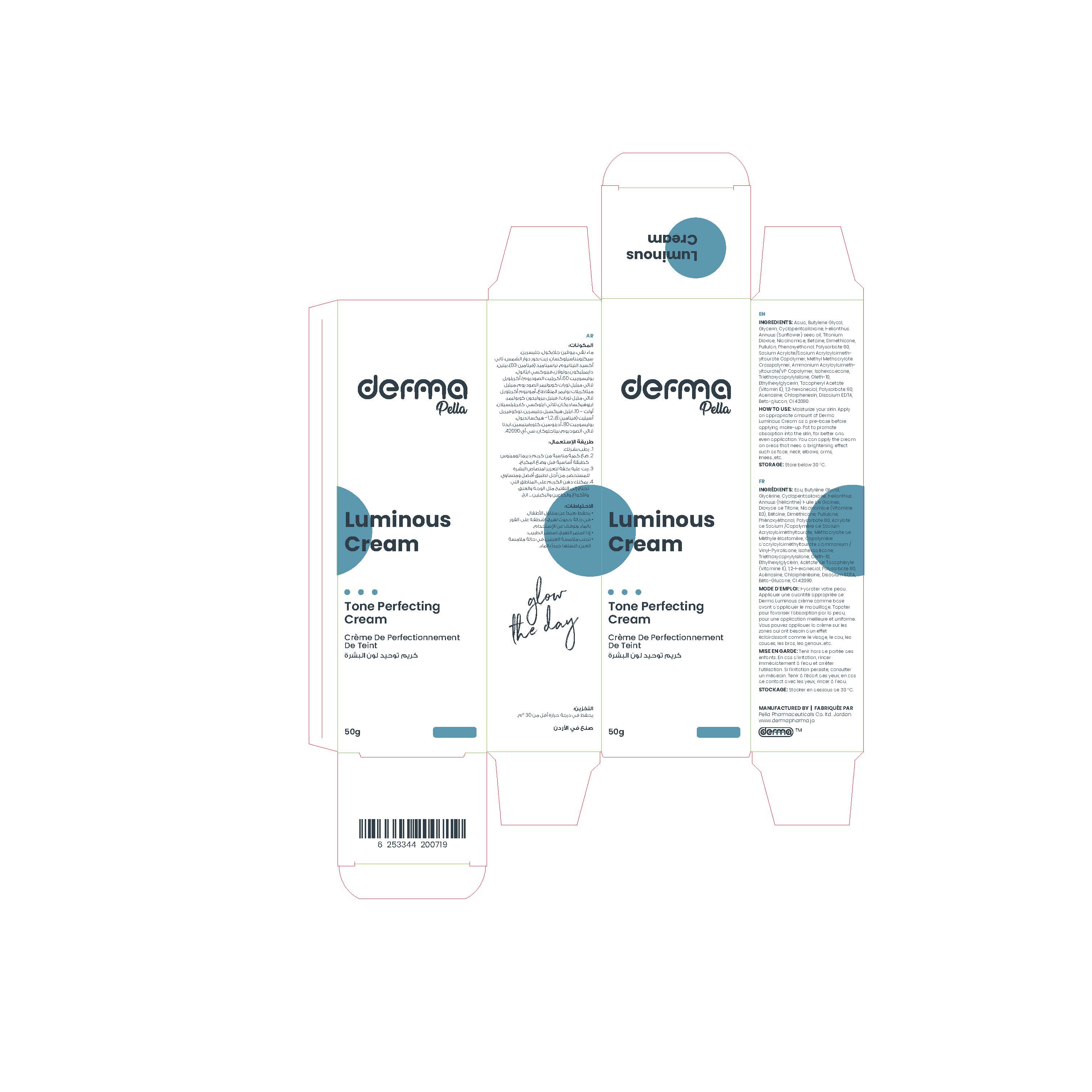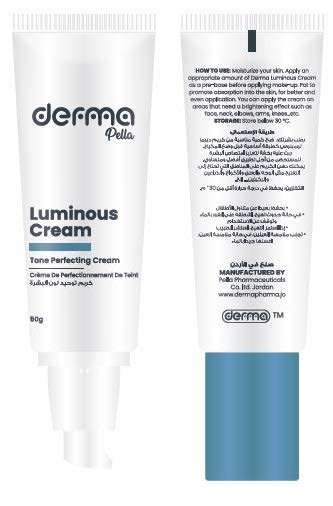 DRUG LABEL: Derma Pella Luminous Cream
NDC: 82160-719 | Form: CREAM
Manufacturer: Pella Pharmaceuticals Co. Ltd
Category: otc | Type: HUMAN OTC DRUG LABEL
Date: 20241231

ACTIVE INGREDIENTS: NIACINAMIDE 20 mg/1 g; ADENOSINE 0.4 mg/1 g; TITANIUM DIOXIDE 28 mg/1 g
INACTIVE INGREDIENTS: DIMETHICONE 100; ETHYLHEXYLGLYCERIN; ALPHA-TOCOPHEROL ACETATE; EDETATE DISODIUM ANHYDROUS; FD&C BLUE NO. 1; CHLORPHENESIN; SUNFLOWER OIL; BETAINE; TRIETHOXYCAPRYLYLSILANE; 1,2-HEXANEDIOL; BUTYLENE GLYCOL; CYCLOMETHICONE 5; SODIUM ACRYLATE/SODIUM ACRYLOYLDIMETHYLTAURATE COPOLYMER (4000000 MW); POLYSORBATE 60; POLYSORBATE 80; PULLULAN; AMMONIUM ACRYLOYLDIMETHYLTAURATE/VP COPOLYMER; WATER; OLETH-10; ISOHEXADECANE; GLYCERIN; PHENOXYETHANOL; METHYL METHACRYLATE/GLYCOL DIMETHACRYLATE CROSSPOLYMER

Luminous Cream

Form and Presentation

Cream: Plastic Tube, 50 g

Active Ingredients

Niacinamide (VitaminB3),Titanium Dioxide, Adenosine

Inactive Ingredients

Aqua, Butylene Glycol, Glycerin, Cyclopentasiloxane, Helianthus Annus (Sunflower) seed oil, Betaine, Dimethicone, Pullulan, Phenoxyethanol, Polysorbate 60, Sodium Acrylate/Sodium Acryloyldimethyltaurate Copolymer, Methyl Methacrylate Crosspolymer, Ammonium Acryloyldimethyltaurate/VP Copolymer, Isohexadance, Triethoxycaprylylsilane, Oleth-10, Ethylhexylglycerin, Tocopheryl Acetate (Vitamin E), 1,2-hexandiol, Polysorbate 80, Chlorphenesin, Disodium EDTA, Beta Glucan, CI 42090.

Purpose

Tone perfecting cream

Properties

Derma Pella Luminous Cream contains a high content of moisturizing base creates dewy skin without dryness and caking and has a refreshing texture that promotes rapid absorption, leaving stickiness-free fresh skin.

Derma Pella Luminous Cream contains Beta Glucan that provides deeper skin moisture and protects skin from external contamination, Derma Pella Luminous cream enriched with Niacinamide (Vitamin B3) offers a natural brightening effect for pure and clear skin, strengthens skin barriers, maintains skin moisture, it also suppresses pigmentation and mitigation. Also contains Adenosine which improves cell regeneration ability and enhancing skin elasticity, helps to improve wrinkles and an anti-inflammatory function.

Paraben Free, Safe for most skin types.

Indications

Derma Pella luminous cream, is a tone-up cream, whitening and wrinkles improving, functional cream that gives an even and bright skin tone.

Give instant brightening flawless glowing complexion with moisture finish.

Precautions

Keep out of reach of children

Warnings

- If irritation occurs, immediately rinse with water and discontinue use.
- If irritation persists, consult with a physician.
- Keep away from your eyes, in case of eye contact, flush with water.

Contraindications

Hypersensitivity to any of the components.

Side Effects

There are no known side effects.

Dosage and Administration

For a perfect finish you have to:

1. moisturize your skin
2. apply an appropriate amount of Derma Luminous Cream as a pre-base before applying make-up
3. pat to promote absorption into the skin, for better and even application.
4. You can apply the cream on areas that need a brightening effect such as face, neck, elbows, arms, knees…etc.

Storage Conditions

Store below 30◦C.